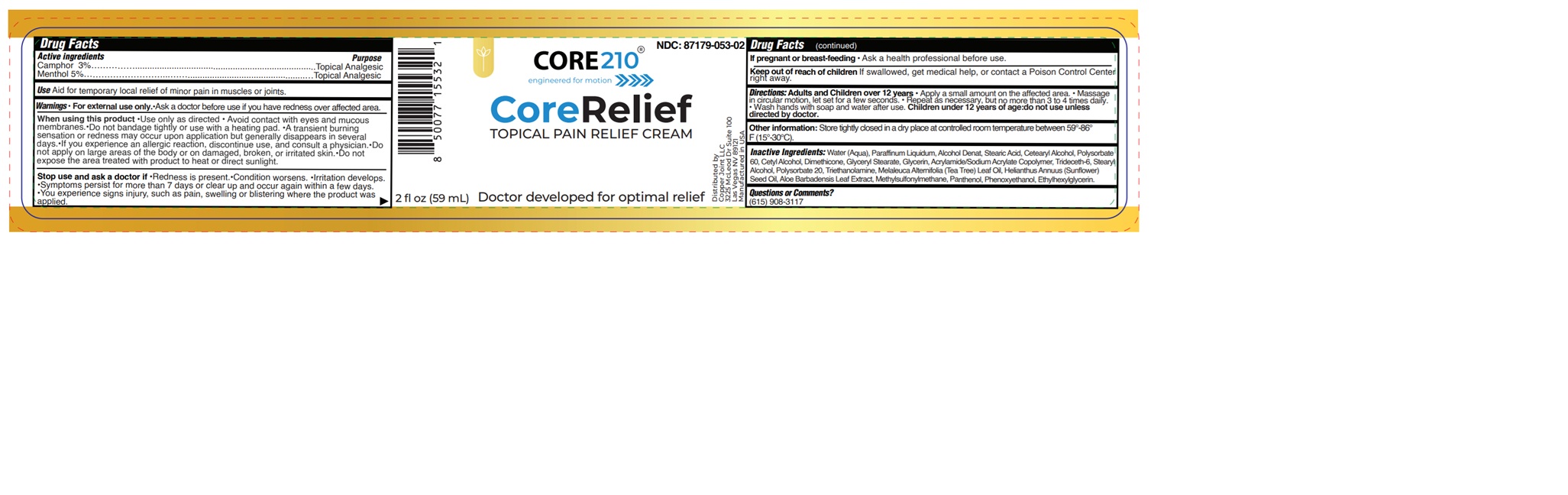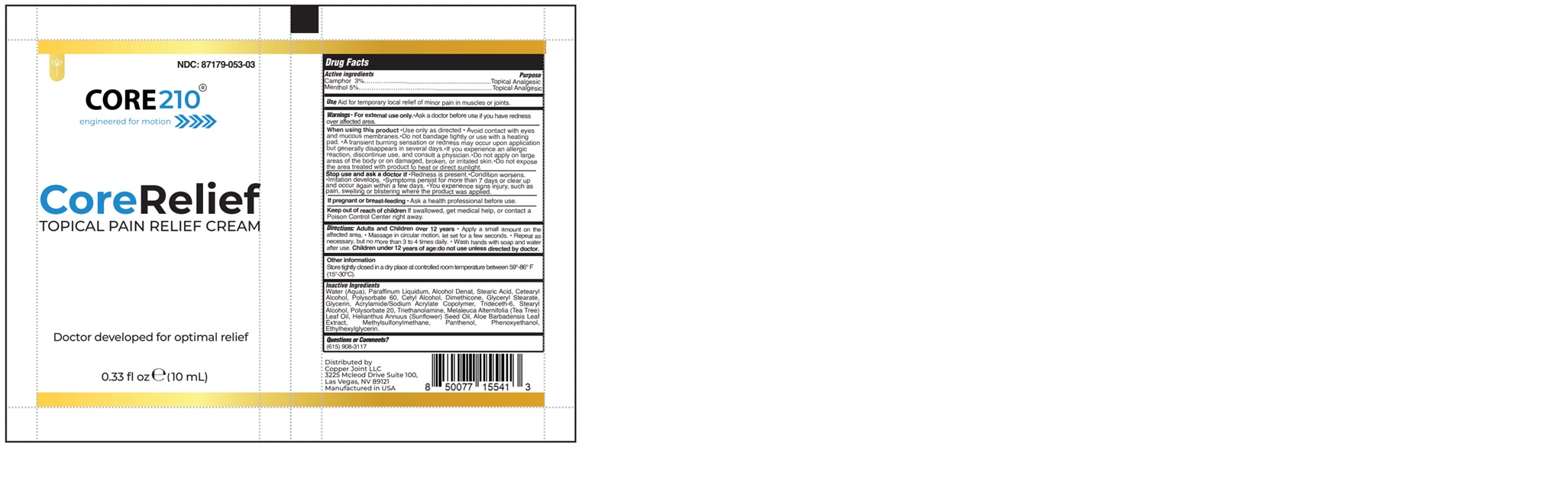 DRUG LABEL: CORE RELIEF
NDC: 87179-053 | Form: CREAM
Manufacturer: Copper Joint, LLC
Category: otc | Type: HUMAN OTC DRUG LABEL
Date: 20251104

ACTIVE INGREDIENTS: CAMPHOR (SYNTHETIC) 3 g/100 mL; MENTHOL 5 g/100 mL
INACTIVE INGREDIENTS: DIMETHYL SULFONE; PHENOXYETHANOL; ALOE VERA LEAF; TRIETHANOLAMINE; MELALEUCA ALTERNIFOLIA (TEA TREE) LEAF OIL; GLYCERIN; DIMETHICONE 1000; STEARYL ALCOHOL; GLYCERYL STEARATE; ALCOHOL; STEARIC ACID; PANTHENOL; CETYL ALCOHOL; ETHYLHEXYLGLYCERIN; PARAFFINUM LIQUIDUM; POLYSORBATE 60; WATER; TRIDECETH-6; POLYSORBATE 20; CETEARYL ALCOHOL; HELIANTHUS ANNUUS (SUNFLOWER) SEED OIL; CARBOMER HOMOPOLYMER TYPE C

87179-053-02
87179-053-03

Active ingredients

Camphor 3%

Menthol 5%

Purpose

Topical Analgesic

Use

Aid for temporary local relief of minor pain in muscles or joints.

Warnings

For external use only.

Ask a doctor before use if you have redness over affected area.

Stop use and ask a doctor if

- Redness is present.
- Condition worsens.
- Irritation develops.
- Symptoms persist for more than 7 days or clear up and occur again within a few days.
- You experience signs injury, such as pain, swelling or blistering where the product was applied.

When using this product

- Use only as directed.
- Avoid contact with eyes and mucous membranes.
- Do not bandage tightly or use with a heating pad.
- A transient burning sensation or redness may occur upon application but generally disappears in several days.
- If you experience an allergic reaction, discontinue use, and consult a physician.
- Do not apply on large areas of the body or on damaged, broken, or irritated skin.
- Do not expose the area treated with product to heat or direct sunlight.

If pregnant or breast – feeding

Ask a health professional before use.

Keep out of reach of children.

If swallowed, get medical help, or contact a Poison Control Center right away.

Directions

Adults and children over 12 years of age

- Apply a small amount to the affected area.
- Massage in a circular motion, let set for a few seconds.
- Repeat as necessary, but no more than 3 to 4 times daily.
- Wash hands with soap and water after use.

Children under 12 years of age:do not use unless directed by doctor.

Other information

Store tightly closed in a dry place at controlled room temperature between 59°F - 86°F (15°C - 30°C)

Inactive ingredients

Water (Aqua), Paraffinum Liquidum, Alcohol Denat, Stearic Acid, Cetearyl Alcohol, Polysorbate 60, Cetyl Alcohol, Dimethicone, Glyceryl Stearate, Glycerin, Acrylamide/Sodium Acrylate Copolymer, Trideceth-6, Stearyl Alcohol, Polysorbate 20, Triethanolamine, Melaleuca Alternifolia (Tea Tree) Leaf Oil, Helianthus Annuus (Sunflower) Seed Oil, Aloe Barbadensis Leaf Extract, Methylsulfonylmethane, Panthenol, Phenoxyethanol, Ethylhexylglycerin.

Questions or comments?

(615)908-3117